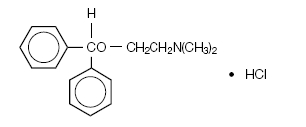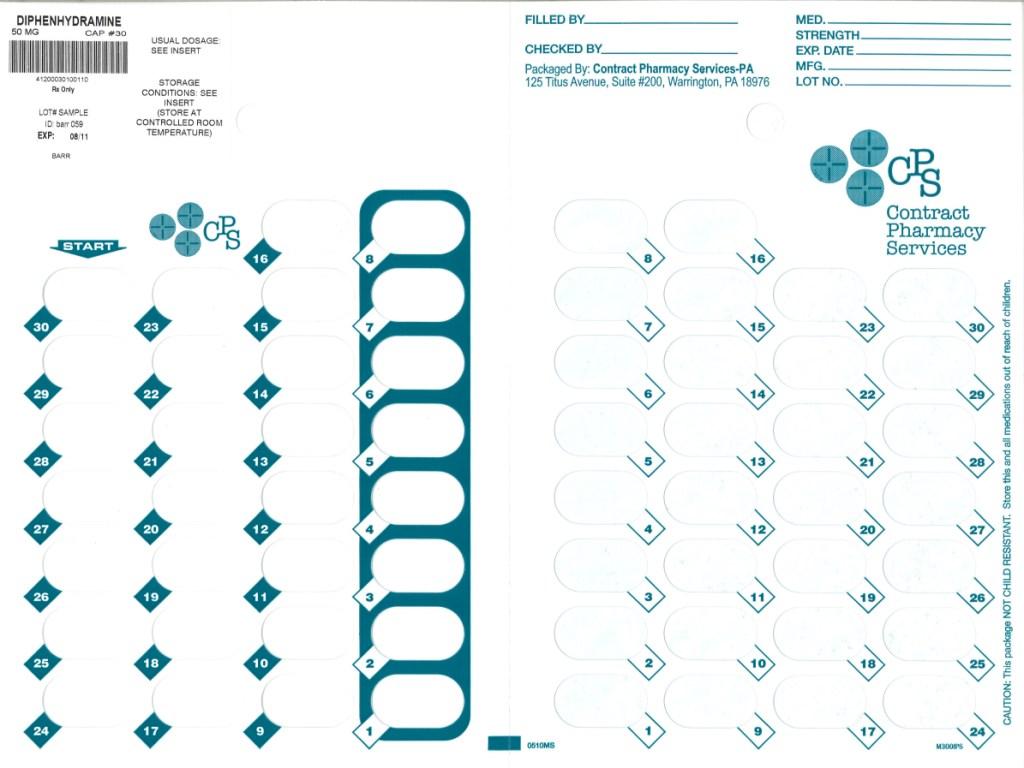 DRUG LABEL: Diphenhydramine Hydrochloride
NDC: 67046-127 | Form: CAPSULE
Manufacturer: Contract Pharmacy Services-PA
Category: prescription | Type: HUMAN PRESCRIPTION DRUG LABEL
Date: 20100805

ACTIVE INGREDIENTS: DIPHENHYDRAMINE HYDROCHLORIDE 50 mg/1 1
INACTIVE INGREDIENTS: ANHYDROUS LACTOSE; D&C RED NO. 28; D&C YELLOW NO. 10; FD&C BLUE NO. 1; FD&C BLUE NO. 1; FD&C BLUE NO. 2; FD&C RED NO. 40; FD&C RED NO. 40; GELATIN; LACTOSE MONOHYDRATE; MAGNESIUM STEARATE; PROPYLENE GLYCOL; SILICON DIOXIDE; SODIUM LAURYL SULFATE; FERROSOFERRIC OXIDE

Diphenhydramine Hydrochloride Capsules, USP

Rx only

DESCRIPTION:

Diphenhydramine Hydrochloride is an antihistamine drug having the chemical name 2-(diphenylmethoxy)-N, N-dimethylethylamine hydrochloride. It occurs as a white, odorless crystalline powder and is freely soluble in water and alcohol. The structural formula is as follows:

C17H21NO • HCl Molecular Weight: 291.82

Each capsule contains 50 mg of diphenhydramine hydrochloride for oral administration.

Inactive Ingredients:

Anhydrous lactose, lactose monohydrate and magnesium stearate.

The 50 mg capsule shell contains D&C red no. 28, FD&C blue no. 1, FD&C red no. 40, gelatin, silicon dioxide and sodium lauryl sulfate.

The imprinting ink contains D&C yellow no. 10 aluminum lake, FD&C blue no. 1 aluminum lake, FD&C blue no. 2 aluminum lake, FD&C red no. 40 aluminum lake, pharmaceutical glaze, propylene glycol and synthetic black iron oxide.

CLINICAL PHARMACOLOGY:

Diphenhydramine hydrochloride is an antihistamine with anticholinergic (drying) and sedative effects. Antihistamines appear to compete with histamine for cell receptor sites on effector cells.

A single oral dose of diphenhydramine hydrochloride is quickly absorbed with maximum activity occurring in approximately one hour. The duration of activity following an average dose of diphenhydramine hydrochloride is from four to six hours. Diphenhydramine is widely distributed throughout the body, including the CNS. Little, if any, is excreted unchanged in the urine; most appears as the degradation products of metabolic transformation in the liver, which are almost completely excreted within 24 hours.

INDICATIONS AND USAGE:

Diphenhydramine hydrochloride in the oral form is effective for the following indications:

Antihistaminic:

For allergic conjunctivitis due to foods; mild, uncomplicated allergic skin manifestations of urticaria and angioedema; amelioration of allergic reactions to blood or plasma; dermatographism; as therapy for anaphylactic reactions adjunctive to epinephrine and other standard measures after the acute manifestations have been controlled.

Motion Sickness:

For active and prophylactic treatment of motion sickness.

Antiparkinsonism:

For parkinsonism (including drug-induced) in the elderly unable to tolerate more potent agents; mild cases of parkinsonism (including drug-induced) in other age groups; in other cases of parkinsonism (including drug-induced) in combination with centrally acting anticholinergic agents.

Nighttime sleep-aid.

CONTRAINDICATIONS:

Use in Newborn or Premature Infants:

This drug should not be used in newborn or premature infants.

Use in Nursing Mothers:

Because of the higher risk of antihistamines for infants generally, and for newborns and prematures in particular, antihistamine therapy is contraindicated in nursing mothers.

Antihistamines are also contraindicated in the following conditions: Hypersensitivity to diphenhydramine hydrochloride and other antihistamines of similar chemical structure.

WARNINGS:

Antihistamines should be used with considerable caution in patients with narrow-angle glaucoma, stenosing peptic ulcer, pyloroduodenal obstruction, symptomatic prostatic hypertrophy, or bladder-neck obstruction.

Use in Children:

In infants and children, especially, antihistamines in overdosage may cause hallucinations, convulsions, or death.

As in adults, antihistamines may diminish mental alertness in children. In the young child, particularly, they may produce excitation.

Use in Elderly (approximately 60 years or older):

Antihistamines are more likely to cause dizziness, sedation, and hypotension in elderly patients.

PRECAUTIONS:

General:

Diphenhydramine hydrochloride has an atropine-like action and therefore should be used with caution in patients with a history of lower respiratory disease including asthma, increased intraocular pressure, hyperthyroidism, cardiovascular disease or hypertension.

Information for Patients:

Patients taking diphenhydramine hydrochloride should be advised that this drug may cause drowsiness and has an additive effect with alcohol.

Patients should be warned about engaging in activities requiring mental alertness such as driving a car or operating appliances, machinery, etc.

Drug Interactions:

Diphenhydramine hydrochloride has additive effects with alcohol and other CNS depressants (hypnotics, sedatives, tranquilizers, etc).

MAO inhibitors prolong and intensify the anticholinergic (drying) effects of antihistamines.

Carcinogenesis, Mutagenesis, Impairment of Fertility:

Long-term studies in animals to determine mutagenic and carcinogenic potential have not been performed.

Pregnancy Category B:

Reproduction studies have been performed in rats and rabbits at doses up to 5 times the human dose and have revealed no evidence of impaired fertility or harm to the fetus due to diphenhydramine hydrochloride. There are, however, no adequate and well-controlled studies in pregnant women. Because animal reproduction studies are not always predictive of human response, this drug should be used during pregnancy only if clearly needed.

ADVERSE REACTIONS:

The most frequent adverse reactions are underscored.

1. General: Urticaria, drug rash, anaphylactic shock, photosensitivity, excessive perspiration, chills, dryness of mouth, nose and throat.
2. Cardiovascular System: Hypotension, headache, palpitations, tachycardia, extrasystoles.
3. Hematologic System: Hemolytic anemia, thrombocytopenia, agranulocytosis.
4. Nervous System: Sedation, sleepiness, dizziness, disturbed coordination, fatigue, confusion, restlessness, excitation, nervousness, tremor, irritability, insomnia, euphoria, paresthesia, blurred vision, diplopia, vertigo, tinnitus, acute labyrinthitis, neuritis, convulsions.
5. GI System: Epigastric distress, anorexia, nausea, vomiting, diarrhea, constipation.
6. GU System: Urinary frequency, difficult urination, urinary retention, early menses.
7. Respiratory System: Thickening of bronchial secretions, tightness of chest and wheezing, nasal stuffiness.

Overdosage:

Antihistamine overdosage reactions may vary from central nervous system depression to stimulation. Stimulation is particularly likely in children. Atropine-like signs and symptoms, dry mouth; fixed, dilated pupils; flushing; and gastrointestinal symptoms may also occur.

If vomiting has not occurred spontaneously the patient should be induced to vomit. This is best done by having him drink a glass of water or milk after which he should be made to gag. Precautions against aspiration must be taken, especially in infants and children.

If vomiting is unsuccessful gastric lavage is indicated within 3 hours after ingestion and even later if large amounts of milk or cream were given beforehand. Isotonic or (½) isotonic saline is the lavage solution of choice.

Saline cathartics, as milk of magnesia, by osmosis draw water into the bowel and therefore are valuable for their action in rapid dilution of bowel content.

Stimulants should not be used.

Vasopressors may be used to treat hypotension.

DOSAGE AND ADMINISTRATION:

DOSAGE SHOULD BE INDIVIDUALIZED ACCORDING TO THE NEEDS AND RESPONSE OF THE PATIENT.

A single oral dose of diphenhydramine hydrochloride is quickly absorbed with maximum activity occurring in approximately one hour. The duration of activity following an average dose of diphenhydramine hydrochloride is from four to six hours.

ADULTS:

25 to 50 mg three or four times daily. The nighttime sleep-aid dosage is 50 mg at bedtime.

CHILDREN:

(over 20 lb): 12.5 to 25 mg three to four times daily. Maximum daily dosage not to exceed 300 mg. For physicians who wish to calculate the dose on the basis of body weight or surface area, the recommended dosage is 5 mg/kg/24 hours or 150 mg/m^2/24 hours.

Data are not available on the use of diphenhydramine hydrochloride as a nighttime sleep-aid in children under 12 years.

The basis for determining the most effective dosage regimen will be the response of the patient to medication and the condition under treatment.

In motion sickness, full dosage is recommended for prophylactic use, the first dose to be given 30 minutes before exposure to motion and similar doses before meals and upon retiring for the duration of exposure.

HOW SUPPLIED:

Diphenhydramine Hydrochloride Capsules, USP are supplied by Contract Pharmacy Services-PA as follows:

NDC | Strength | Quantity/Form | Color | Source Prod. Code
67046-127-30 | 50 mg | 30 Capsules in a Blister Pack | PINK | 0555-0059

Store at controlled room temperature 15°-30°C (59°-86°F).

MANUFACTURED BY
BARR LABORATORIES, INC.
POMONA, NY 10970

Repackaged by:
Contract Pharmacy Services-PA
125 Titus Ave Suite 200
Warrington, PA 18976 USA

Original--08/2010--NJW

Label Image 50 mg

50 mg Capsules